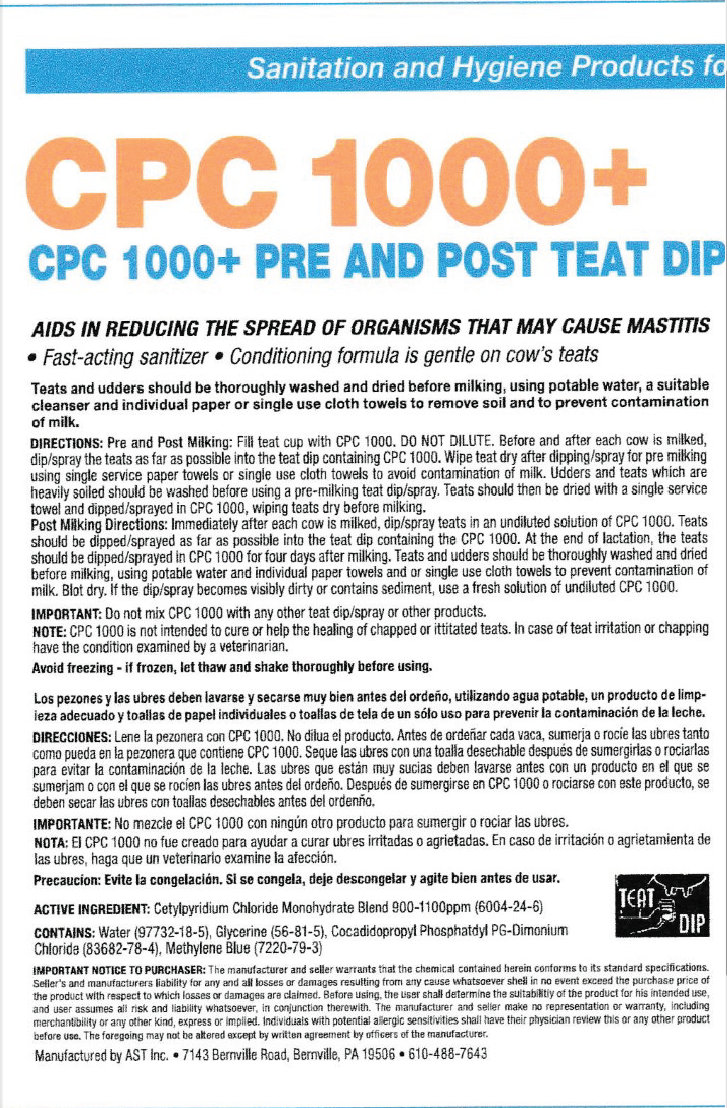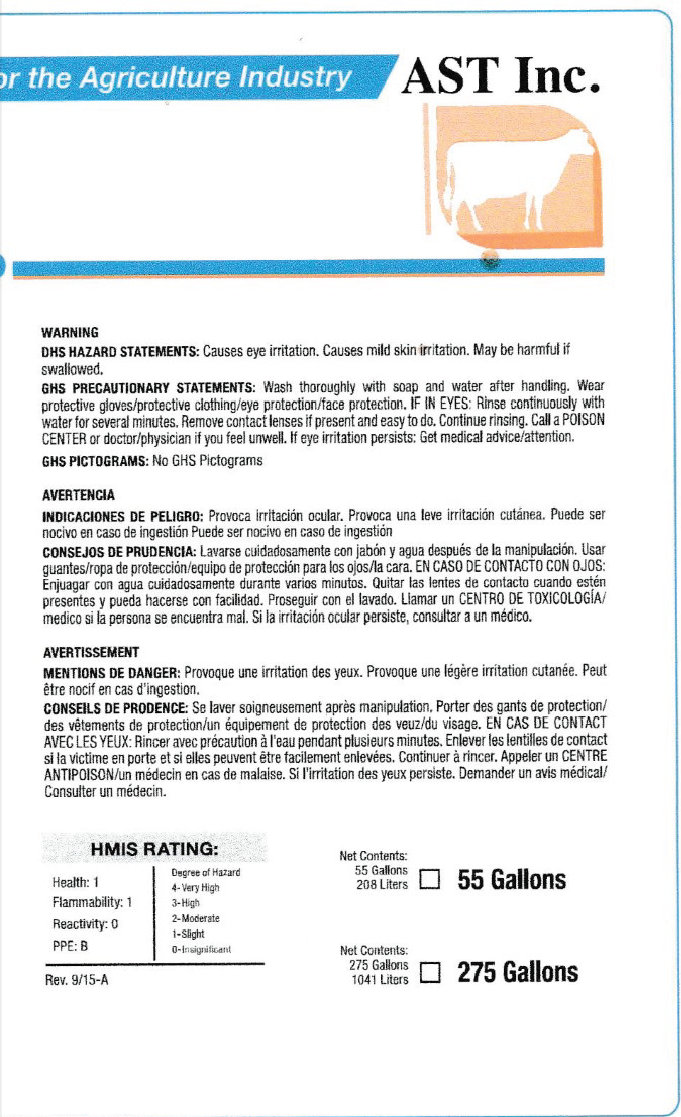 DRUG LABEL: CPC 1000 Pre and Post Teat Dip
NDC: 52657-0011 | Form: LIQUID
Manufacturer: Advanced Skin Technologies, Inc.
Category: animal | Type: OTC ANIMAL DRUG LABEL
Date: 20170228

ACTIVE INGREDIENTS: CETYLPYRIDINIUM CHLORIDE 1000 [ppm]/1 L

CPC 1000 Pre and Post Teat Dip